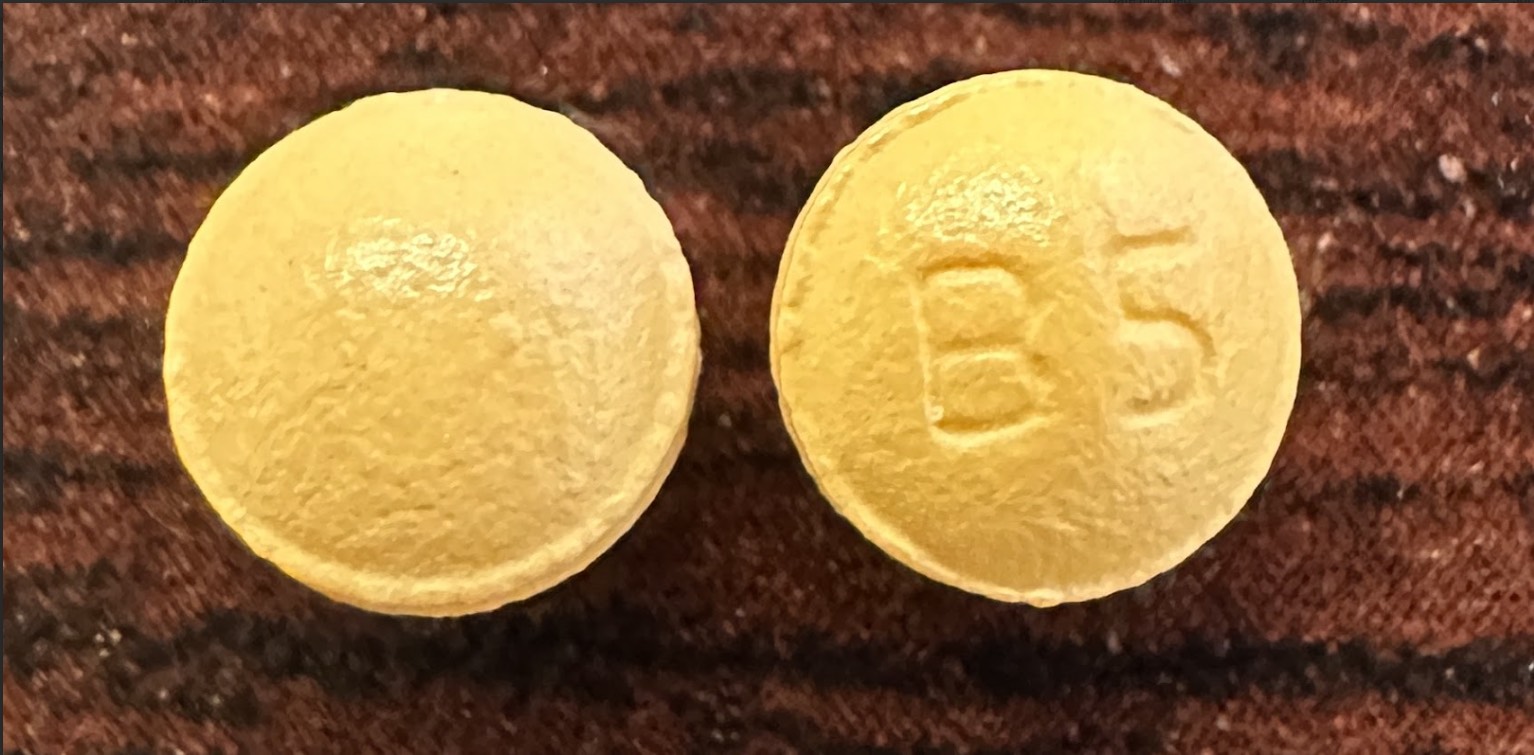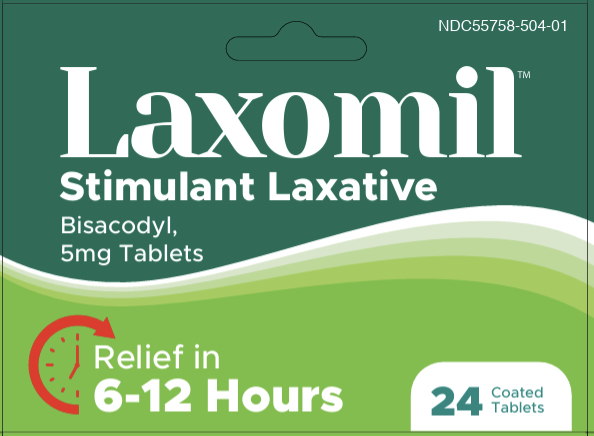 DRUG LABEL: Laxomil
NDC: 55758-504 | Form: TABLET, COATED
Manufacturer: Pharmadel LLC
Category: otc | Type: HUMAN OTC DRUG LABEL
Date: 20250710

ACTIVE INGREDIENTS: BISACODYL 5 mg/1 1
INACTIVE INGREDIENTS: D&C YELLOW NO. 10; FD&C YELLOW NO. 6; HYPROMELLOSE, UNSPECIFIED; MAGNESIUM STEARATE; POLYETHYLENE GLYCOL, UNSPECIFIED; TALC; TITANIUM DIOXIDE; SILICON DIOXIDE; WATER; METHACRYLIC ACID; MALTODEXTRIN; MICROCRYSTALLINE CELLULOSE; SODIUM STARCH GLYCOLATE TYPE A; TRIETHYL CITRATE

Laxomil (HHH)

Active ingredients and Purposes

Active ingredientes (in each tablet) | Purpose
Bisacodyl 5 mg ......... | Stimulant laxative

Use

For relief of occasional constipation (irregularity). This product generally produces bowel movement in 6 to 12 hours.

Warnings

Do not use

- if you cannot swallow without chewing. These tablets should not be chewed because gastric irritation may occur.

Ask a doctor before use if you have

- abdominal pain, nausea, or vomiting
- noticed a sudden change in bowel habits that persists over a period of 2 weeks

When using this product

- take this product 2 hours before or after other drugs
- do not take this product within 1 hour after taking an antacid or milk

Stop use and ask a doctor if

- you need to use for more than 7 days
- rectal bleeding occurs
- you fail to have a bowel movement after use of a laxative. This may indicate a serious condition.

If pregnant or breast-feeding,

ask a health professional before use

Keep out of reach of children

In case of overdose, get medical help or contact a Poison Control Center right away.

Directions

- take with plenty of water
- do not chew or crush tablet(s)

Age | Dose
adults and children 12 years and older | take 1 to 3 tablets in a single dose, once a day
children 6 to undee 12 years | take 1 tablet once a day
children under 6 years | consult a doctor

Other information

- store between 68-77°F (20-25°C)
- do not use if seal under cap is torn, broken or missing

Inactive ingredients

D&C yellow #10, FD&C yellow #6, hypromellose, magnesium stearate, maltodextrin, methacrylic acid, microcrystalline cellulose, polyethylene glycol, silicon dioxide, sodium starch glycolate type A, talc, titanium dioxide,triethyl citrate, water

Questions?

+1-866-359-3478 (M-F) 9 AM - 5 PM EST or www.pharmadel.com

Dist. by/ por:

Pharmadel LLC

New Castle, DE 19720

+1-866-359-3478

www.pharmadel.com